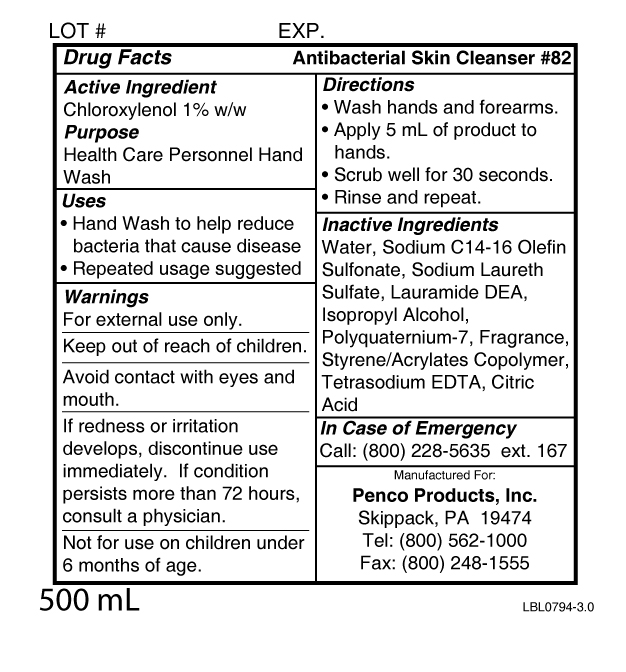 DRUG LABEL: Antibacterial Skin Cleanser 82
NDC: 42497-822 | Form: SOAP
Manufacturer: Penco Products, Inc.
Category: otc | Type: HUMAN OTC DRUG LABEL
Date: 20100304

ACTIVE INGREDIENTS: Chloroxylenol 1 g/100 g
INACTIVE INGREDIENTS: Water; Sodium Laureth Sulfate; Isopropyl Alcohol; Edetate Sodium; Citric Acid Monohydrate; Lauric Diethanolamide; Sodium C14-16 Olefin Sulfonate

Active Ingredient
Chloroxylenol 1% w/w

Purpose
Health Care Personnel Hand Wash

Uses

- Hand Wash to help reduce bacteria that cause disease
- Repeated usage suggested

Warnings
For external use only.
Keep out of reach of children.
Avoid contact with eyes and mouth.
If redness or irritation develops, discontinue use immediately. If condition persists for more than 72 hours, consult a physician.
Not for use on children under 6 months of age.

Directions

- Wash hands and forearms.
- Apply 5 mL of product to hands.
- Scrub well for 30 seconds.
- Rinse and repeat.

Inactive Ingredients
Water, Sodium C14-16 Olefin Sulfonate, Sodium Laureth Sulfate, Lauramide DEA, Isopropyl Alcohol, Polyquaternium-7, Fragrance, Styrene Acrylates/Copolymer, Tetrasodium EDTA, Citric Acid

QUESTIONS

In Case of Emergency
Call: (800) 228-5635 ext. 167